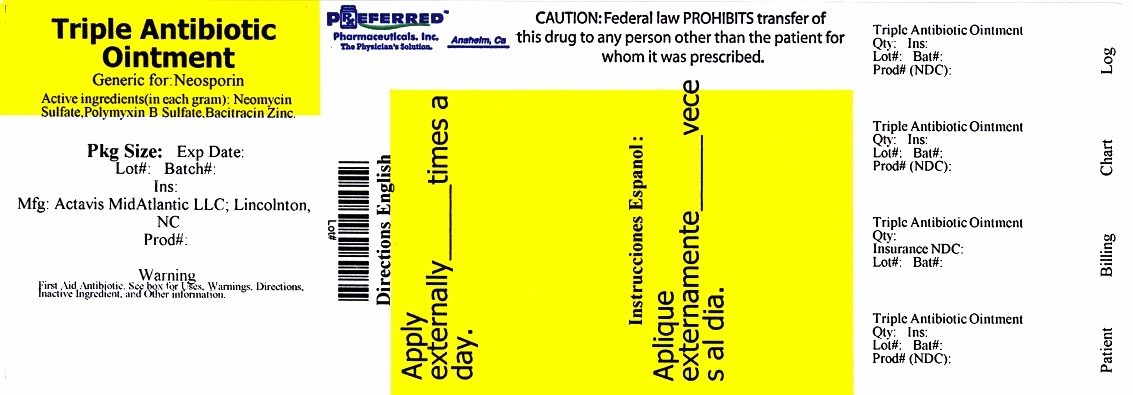 DRUG LABEL: TRIPLE ANTIBIOTIC
NDC: 68788-9811 | Form: OINTMENT
Manufacturer: Preferred Pharmaceuticals, Inc
Category: otc | Type: HUMAN OTC DRUG LABEL
Date: 20120425

ACTIVE INGREDIENTS: BACITRACIN ZINC 400 [iU]/1 g; NEOMYCIN SULFATE 3.5 mg/1 g; POLYMYXIN B SULFATE 5000 [iU]/1 g
INACTIVE INGREDIENTS: PETROLATUM

Bacitracin Zinc, Neomycin Sulfate, Polymyxin B Sulfate Ointment

ACTIVE INGREDIENTS

(in each gram)

Bacitracin zinc, USP 400 units

Neomycin sulfate, USP 3.5 mg

Polymyxin B sulfate, USP 5,000 units

PURPOSE

First aid antibiotic

USES

Helps prevent infection in

- minor cuts
- scrapes
- burns

WARNINGS

For external use only

Allergy alert:

- do not use if allergic to any of the ingredients

DO NOT USE

- in the eyes
- over large areas of the body

ASK A DOCTOR BEFORE USE IF YOU HAVE

- deep or puncture wounds
- animal bites
- serious burns

WHEN USING THIS PRODUCT

- do not use longer than 1 week unless directed by a doctor

STOP USE AND ASK A DOCTOR IF

- condition persists or gets worse
- a rash or other allergic reaction develops

KEEP OUT OF REACH OF CHILDREN.

If swallowed, get medical help or contact a Poison Control Center right away.

DIRECTIONS

- clean affected area
- apply a small amount (equal to the surface area of the tip of a finger) on the area 1 to 3 times daily
- may be covered with a sterile bandage

Other Information

- Store at controlled room temperature 59º - 86ºF (15º - 30ºC).
- Protect from freezing.

INACTIVE INGREDIENT

White petrolatum

HOW SUPPLIED

Triple Antibiotic Ointment comes in 28gr tubes

NDC - 68788-9811-2

QUESTIONS?

1-800-432-8534 between 9 am and 4 pm EST, Monday – Friday.

Relabeled By Preferred Pharmaceuticals, Inc